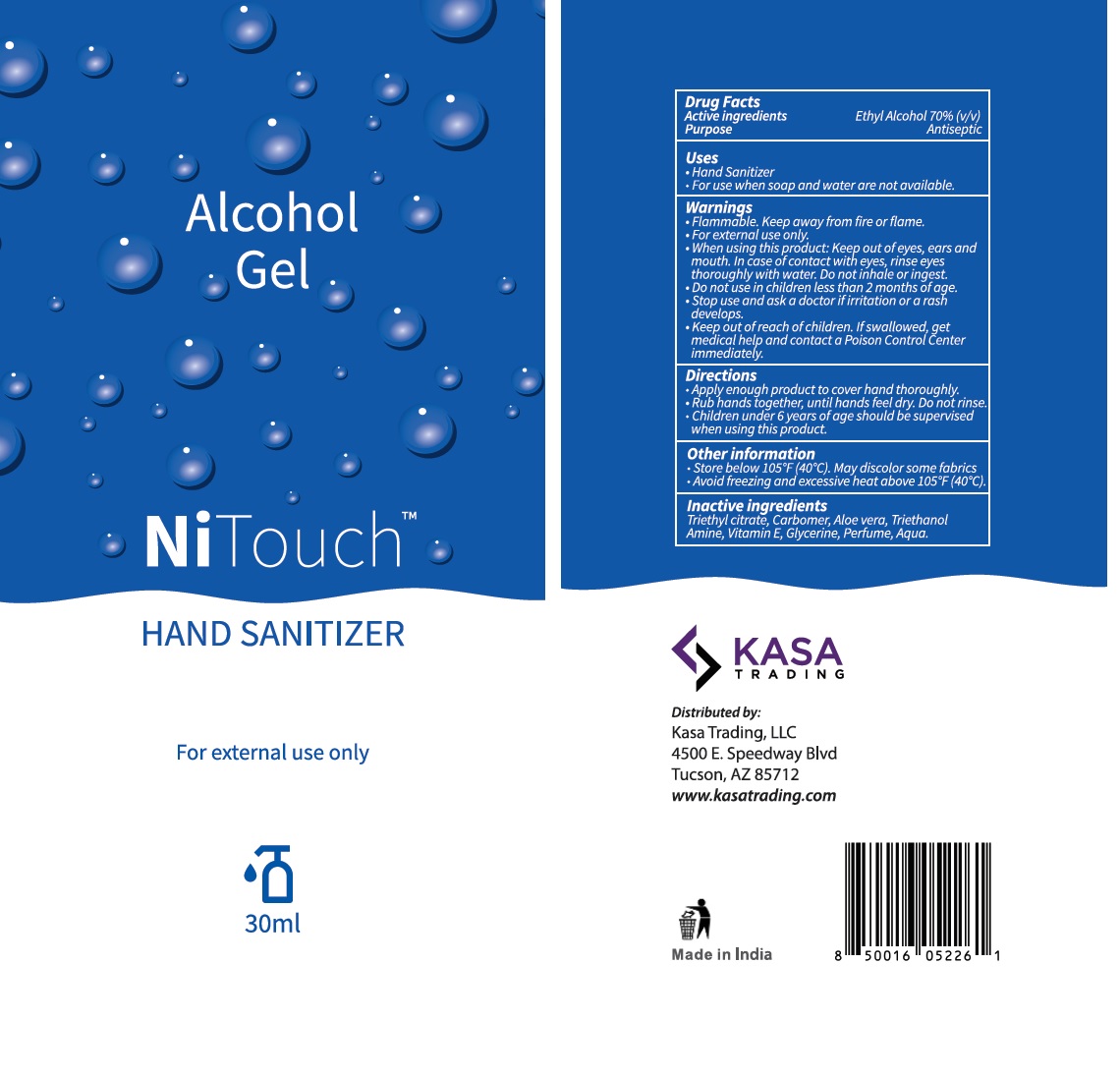 DRUG LABEL: NiTouch Hand Sanitizer
NDC: 80437-010 | Form: GEL
Manufacturer: Kasa Trading, Llc
Category: otc | Type: HUMAN OTC DRUG LABEL
Date: 20210406

ACTIVE INGREDIENTS: ALCOHOL 70 mL/100 mL
INACTIVE INGREDIENTS: TRIETHYL CITRATE; CARBOMER HOMOPOLYMER, UNSPECIFIED TYPE; ALOE VERA LEAF; TROLAMINE; .ALPHA.-TOCOPHEROL; GLYCERIN; WATER

NiTouchTM HAND SANITIZER

Active ingredients

Ethyl Alcohol 70% (v/v)

Purpose

Antiseptic

Uses

• Hand Sanitizer
• For use when soap and water are not available.

Warnings

• Flammable. Keep away from fire or flame.
• For external use only.
• When using this product: Keep out of eyes, ears and mouth. In case of contact with eyes, rinse eyes thoroughly with water. Do not inhale or ingest.
• Do not use in children less than 2 months of age.
• Stop use and ask a doctor if irritation or a rash develops.

• Keep out of reach of children. If swallowed, get medical help and contact a Poison Control Center immediately.

Directions

• Apply enough product to cover hand thoroughly.
• Rub hands together, until hands feel dry. Do not rinse.
• Children under 6 years of age should be supervised when using this product.

Other information

• Store below 105°F (40°C). May discolor some fabrics
• Avoid freezing and excessive heat above 105°F (40°C).

Inactive ingredients

Triethyl citrate, Carbomer, Aloe vera, Triethanolamine, Vitamin E, Glycerin, Parfum, Aqua

Alcohol Gel

KASA TRADING

Distributed by:
Kasa Trading, LLC
4500 E. Speedway Blvd
Tucson, AZ 85712
www.kasatrading.com

Made in India